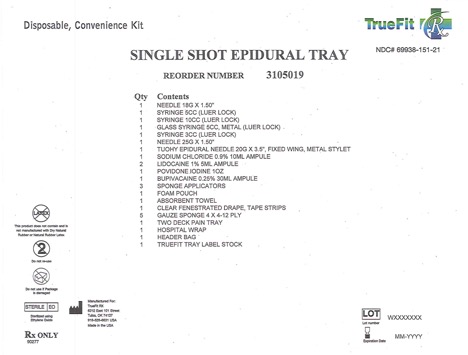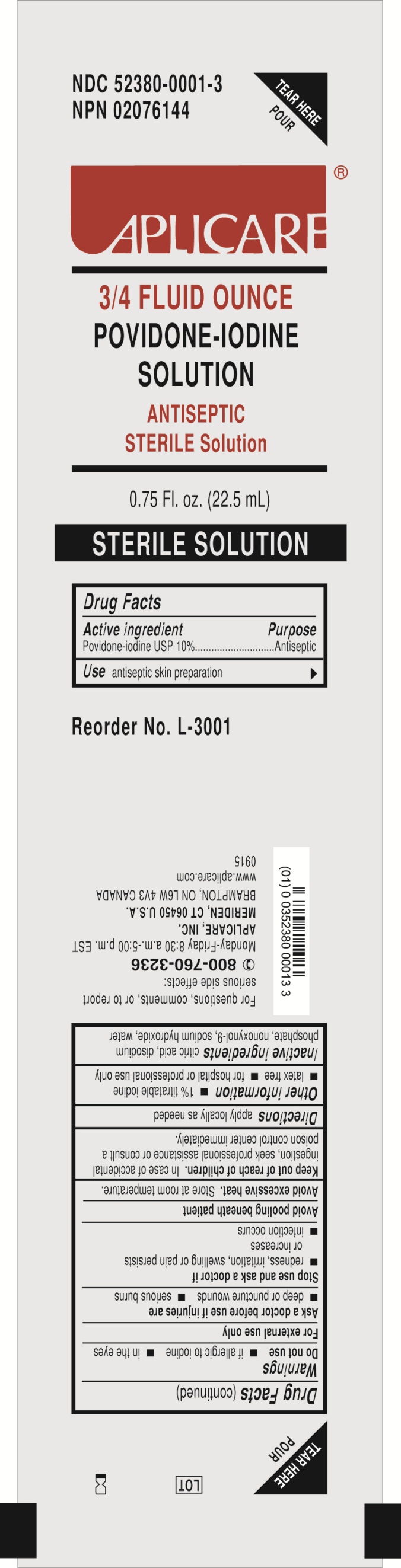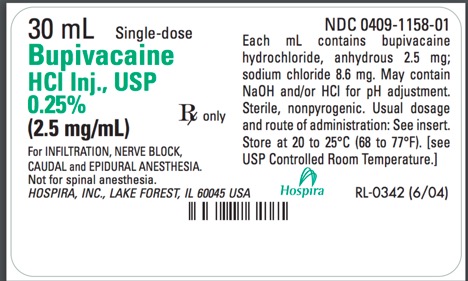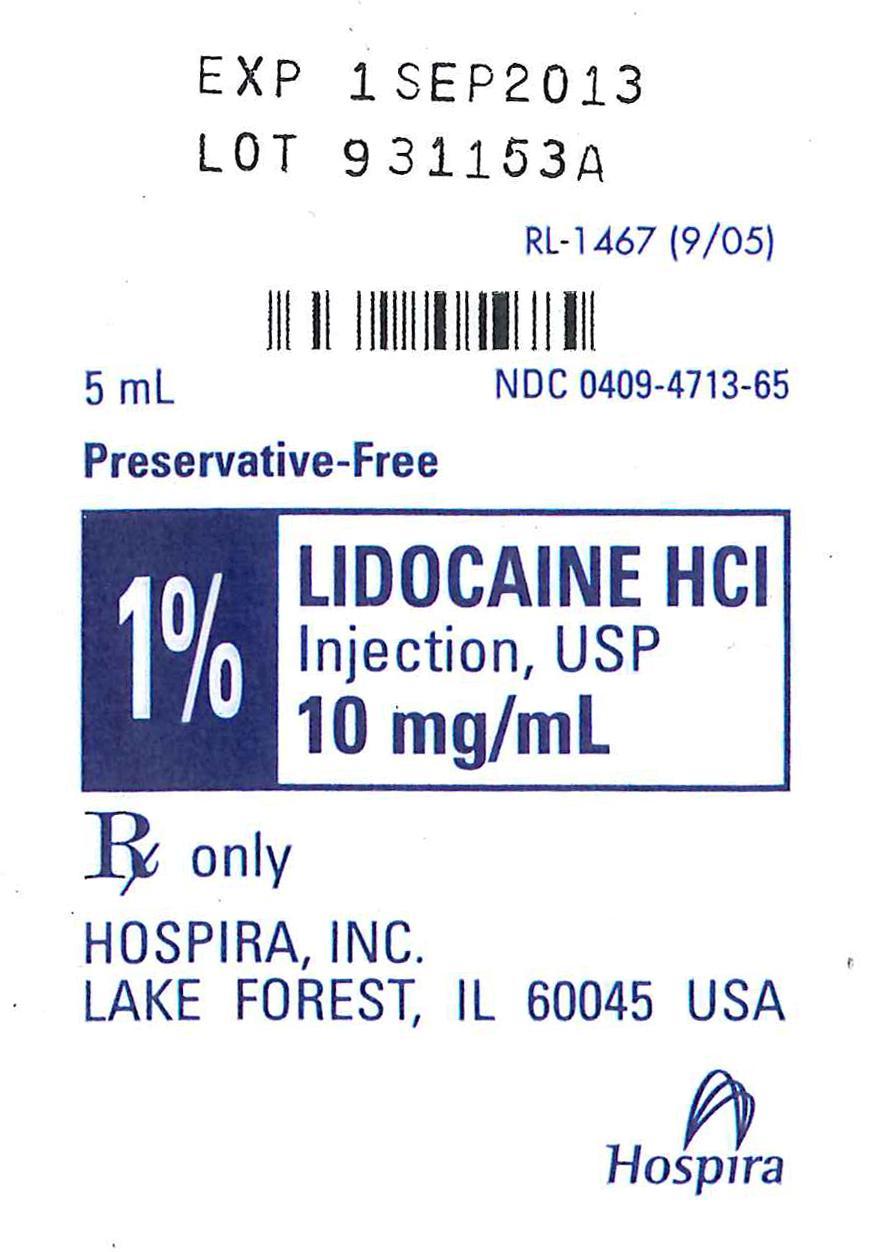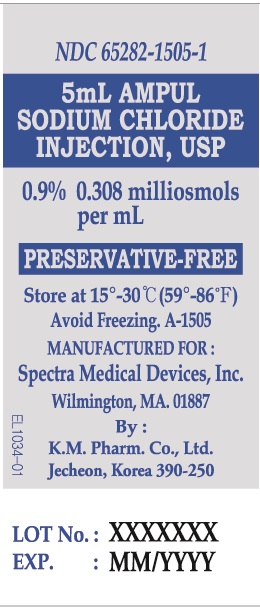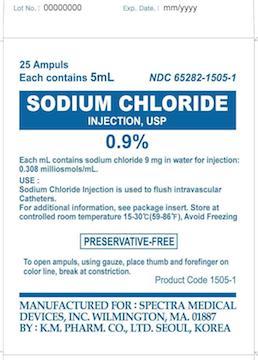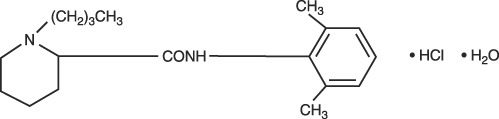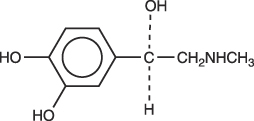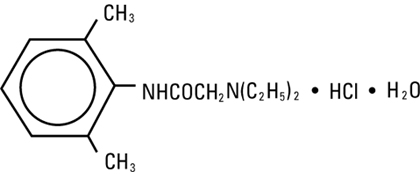 DRUG LABEL: Disposable Convenience Kit (Single Shot Epidural)
NDC: 69938-153 | Form: KIT | Route: EPIDURAL
Manufacturer: True Fit RX LLC
Category: prescription | Type: HUMAN PRESCRIPTION DRUG LABEL
Date: 20160209

ACTIVE INGREDIENTS: SODIUM CHLORIDE 9 mg/1 mL; POVIDONE-IODINE 0.1 mg/1 mL; BUPIVACAINE HYDROCHLORIDE 2.5 mg/1 mL; LIDOCAINE HYDROCHLORIDE 10 mg/1 mL
INACTIVE INGREDIENTS: WATER; CITRIC ACID MONOHYDRATE; SODIUM PHOSPHATE, DIBASIC; NONOXYNOL-9; WATER; SODIUM CHLORIDE; SODIUM HYDROXIDE; WATER; HYDROCHLORIC ACID; HYDROCHLORIC ACID; SODIUM CHLORIDE 7 mg/1 mL; SODIUM HYDROXIDE; WATER

Disposable Convenience Kit (Single Shot Epidural)

DESCRIPTION

BUPIVACAINE HYDROCHLORIDE injection, solution
BUPIVACAINE HYDROCHLORIDE AND EPINEPHRINE (bupivacaine hydrochloride and epinephrine bitartrate) injection, solution
[Hospira, Inc.]

Rx only

THE 0.75% CONCENTRATION OF BUPIVACAINE HYDROCHLORIDE IS NOT RECOMMENDED FOR OBSTETRICAL ANESTHESIA.

THERE HAVE BEEN REPORTS OF CARDIAC ARREST WITH DIFFICULT RESUSCITATION OR DEATH DURING USE OF BUPIVACAINE HYDROCHLORIDE FOR EPIDURAL ANESTHESIA IN OBSTETRICAL PATIENTS. IN MOST CASES, THIS HAS FOLLOWED USE OF THE 0.75% CONCENTRATION. RESUSCITATION HAS BEEN DIFFICULT OR IMPOSSIBLE DESPITE APPARENTLY ADEQUATE PREPARATION AND APPROPRIATE MANAGEMENT. CARDIAC ARREST HAS OCCURRED AFTER CONVULSIONS RESULTING FROM SYSTEMIC TOXICITY, PRESUMABLY FOLLOWING UNINTENTIONAL INTRAVASCULAR INJECTION. THE 0.75% CONCENTRATION SHOULD BE RESERVED FOR SURGICAL PROCEDURES WHERE A HIGH DEGREE OF MUSCLE RELAXATION AND PROLONGED EFFECT ARE NECESSARY.

DESCRIPTION

Bupivacaine Hydrochloride is 2-Piperidinecarboxamide, 1-butyl-N-(2,6-dimethylphenyl)-, monohydrochloride, monohydrate, a white crystalline powder that is freely soluble in 95 percent ethanol, soluble in water, and slightly soluble in chloroform or acetone. It has the following structural formula:

bupivacaine hydrochloride 1

Epinephrine is (-)-3,4-Dihydroxy-α-[(methylamino)methyl] benzyl alcohol. It has the following structural formula:

bupivacaine hydrochloride 2

infiltration, peripheral nerve block, and caudal and lumbar epidural blocks. Solutions of Bupivacaine Hydrochloride may be autoclaved if they do not contain epinephrine. Solutions are clear and colorless.

Bupivacaine is related chemically and pharmacologically to the aminoacyl local anesthetics. It is a homologue of mepivacaine and is chemically related to lidocaine. All three of these anesthetics contain an amide linkage between the aromatic nucleus and the amino, or piperidine group. They differ in this respect from the procaine-type local anesthetics, which have an ester linkage.

Bupivacaine Hydrochloride Injection, USP is available in sterile, isotonic solutions containing bupivacaine hydrochloride in water for injection with characteristics as follows:

Buivacaine Hydrochloride Injection USP (without epinephrine)
Concentration | Bupivacaine Hydrochloride mg/ml | Sodium Chloride mg/ml
0.25% | 2.5 | 8.6
0.5% | 5 | 8.1
0.75% | 7.5 | 7.6

May contain sodium hydroxide and/or hydrochloric acid for pH adjustment. (See HOW SUPPLIED section for pH information.) Multiple-dose vials contain methylparaben 1 mg/mL added as a preservative.

Bupivacaine and Epinephrine Injection, USP is available in sterile, isotonic solutions containing bupivacaine hydrochloride and epinephrine 1:200,000 with characteristics as follows:

Bupivacaine and Epinephrine Injection, USP
Concentration (Bupivacaine HCL) | Bupivacaine Hydrochloride (mg/ml) | Epinephrine 1:2000,000 (mcg/ml) | Sodium Chloride (mg/ml)
0.25% | 2.5 | 5 | 8.5
0.5% | 5 | 5 | 8.5
0.75% | 7

Sodium metabisulfite 0.1 mg/mL added as antioxidant and edetate calcium disodium, anhydrous 0.1 mg/mL added as stabilizer. May contain sodium hydroxide and/or hydrochloric acid for pH adjustment. (See HOW SUPPLIED section for pH information.) Multiple-dose vials contain methylparaben 1 mg/mL added as a preservative.

Single-dose solutions contain no added bacteriostat or anti-microbial agent and unused portions should be discarded after use.

HOW SUPPLIED

0.25% 30ML Ampule

DESCRIPTION

APLICARE POVIDONE-IODINE SOLUTION (povidone-iodine solution) solution
3/4 FLUID OUNCE

Povidone-iodine 10%
Antiseptic

Warnings

Do not use:

- if allergic to iodine
- in the eyes

For external use only

Ask a doctor before use if injuries are

- deep or puncture wounds
- serious burns

Stop use and ask a doctor if

- redness, irritation, swelling or pain persists or
- increases infection occurs

Avoid pooling beneath patient

Keep out of reach of children.

In case of accidental ingestion, seek professional assistance or consult a poison control center immediately.

Aplicare Povidone Iodine PDP

DESCRIPTION

LIDOCAINE HYDROCHLORIDE (lidocaine hydrochloride anhydrous) injection, solution

AQUEOUS SOLUTIONS FOR INFILTRATION

AND NERVE BLOCK

Ampul

Plastic Multiple-dose Fliptop Vial

Glass Teartop Vial

Rx only

DESCRIPTION
Lidocaine Hydrochloride Injection, USP is a sterile, nonpyrogenic solution of lidocaine hydrochloride in water for injection for parenteral administration in various concentrations with characteristics as follows:

Concentration | 0.5% | 1% | 1.5% | 2%
mg/ml lidocaine HCL (anhyd.) | 5 | 10 | 15 | 20
mg/ml sodium chloride | 8 | 7 | 6

Multiple-dose vials contain 0.1% of methylparaben added as preservative. May contain sodium hydroxide and/or hydrochloric acid for pH adjustment. The pH is 6.5 (5.0 to 7.0). See HOW SUPPLIED section for various sizes and strengths.

Lidocaine is a local anesthetic of the amide type.

Lidocaine Hydrochloride, USP is chemically designated 2-(diethylamino)-N-(2,6-dimethylphenyl)-acetamide monohydrochloride monohydrate, a white powder freely soluble in water. The molecular weight is 288.82. It has the following structural formula:

lidocaine hydrochloride injection figure

The semi-rigid vial used for the plastic vials is fabricated from a specially formulated polyolefin. It is a copolymer of ethylene and propylene. The safety of the plastic has been confirmed by tests in animals according to USP biological standards for plastic containers. The container requires no vapor barrier to maintain the proper drug concentration.

DESCRIPTION

Disposable, Convenience Kit (Single Shot Epidural Tray)

Kit Contains:

DESCRIPTION

Sodium Chloride Injection, USP is a sterile, nonpyrogenic, isotonic solution of sodium chloride 0.9% (9 mg/mL) in Water for Injection containing no antimicrobial agent or other added substance. The pH is between 4.5 and 7.0. Its chloride and sodium ion concentrates are approximately 0.154 mEq of each per milliliter and its calculated osmolality is 0.308 milliosmols per mL.

Sodium chloride occurs as colorless cubic crystals or white crystalline powder and has a saline taste.
Sodium Chloride is freely soluble in water. It is soluble in glycerin and slightly soluble in alcohol. The empirical formula for sodium chloride is NaCl, and the molecular weight is 58.44.

CLINICAL PHARMACOLOGY

Sodium chloride comprises over 90% of the inorganic constituents of the blood serum. Sodium
chloride in water dissociates to provide sodium (Na+) and chloride (Cl-) ions. These ions are normal
constituents of the body fluids (principally extracellular) and are essential for maintaining electrolyte balance. The small volume of Fluid and amount of sodium chloride provided by Sodium Chloride Injection, USP, 0.9% when used only as a vehicle for parenteral injection of drugs, is unlikely to exert a significant effect on fluid and electrolyte balance except possibly in very small infants.

WARNINGS

Sodium Chloride must be used with caution in the presence of congestive heart failure, circulatory
insufficiency, kidney dysfunction or hypoproteinemia. Excessive amounts of sodium chloride by any route may cause hypokalemia and acidosis.

Excessive amounts by parental routes may precipitate congestive heart failure and acute pulmonary edema, especially seen in patients with preexisting cardiovascular disease and those receiving corticos-teroids, corticotropin or other drugs that may give rise to sodium retention. For use in newborns, when a Sodium Chloride solution is required for preparation or diluting medications,
or in flushing intravenous catheters, only preservative-free Sodium Chloride Injection, USP,
0.9% should be used.

INDICATIONS AND USAGE

Sodium Chloride Injection is used to flush intravascular catheters or as a sterile, isotonic single dose vehicle, solvent, or diluent for substances to be administered intravenously, intramuscularly or subcutaneously and for other extemporaneously prepared single dose sterile solutions according to
instructions of the manufacture of the drug to be administered.

PRECAUTIONS

Since Sodium Chloride Injection does not contain antimicrobial agents and is intended for single use,
any unused amount must be discarded immediately following withdrawal of any portion of the contents
of the vial or ampul. Do not open ampul until it is to be used.

Consult the manufactures instructions for choice of vehicle, appropriate dilution or volume for
dissolving the drug to be injected, including the route and rate of injection.

PREGNANCY

Pregnancy Category C: Animal reproductive studies have not been conducted with Sodium Chloride
Injection USP 0.9%. It is also not known whether Sodium Chloride Injection USP 0.9% can cause fetal
harm when administered to a pregnant woman or can affect reproduction capacity. Sodium Chloride
Injection USP 0.9% should be given to a pregnant woman only if clearly needed.

ADVERSE REACTIONS

Reactions which may occur because of this solution, added drugs or the technique of reconstitution or
administration include febrile response, local tenderness, abscess, tissue necrosis or infection at the site of injection, venous thrombosis or phlebitis extending from the site of injection and extravasation.

If an adverse reaction does occur, discontinue the infusion, evaluate the patient, institute appropriate
countermeasures, and if possible, retrieve and save the remainder of the unused vehicle for examination.

OVERDOSAGE

When used as a diluent, solvent or intravascular flushing solution, this parental preparation is unlikely to pose a threat of sodium chloride or fluid overload except possible in very small infants. In the event these should occur, reevaluate the patient and institute appropriate corrective measures.

DOSAGE AND ADMINISTRATION

Before Sodium Chloride Injection, USP, 0.9% is used as a vehicle for the administration of a drug,
specific references should be checked for any possible incompatibility with sodium chloride. The
volume of the preparation to be used for diluting or dissolving any drug for injection is dependent on
the vehicle concentration, dose and route of administration as recommended by the manufacture.
Sodium Chloride Injection, USP, 0.9% is also indicated for use in flushing intravenous catheters.

Prior to and after administration of the medication, the intravenous catheter should be flushed in its entirety with Sodium Chloride Injection, USP, 0.9%. Use in accord with any warnings or precautions appropriate to the medication being administered. Parental drug products should be inspected visually for particulate matter and discoloration prior to administration, whenever solution and container permit.

INSTRUCTIONS FOR USE

To open ampuls, using gauze, place thumb and forefinger on color line, break at constriction.

HOW SUPPLIED

0.9% 10ML ampule

STORAGE AND HANDLING

Store at controlled room temperature 15-30 C (59-86 F). Avoid freezing.

Manufactured for:

Spectra Medical Devices, Inc. 260-F Fordham Road, Wilmington, MA 01887
By: KM. Pharm. Co., LTD.
SM1500 Rev. B 12/00